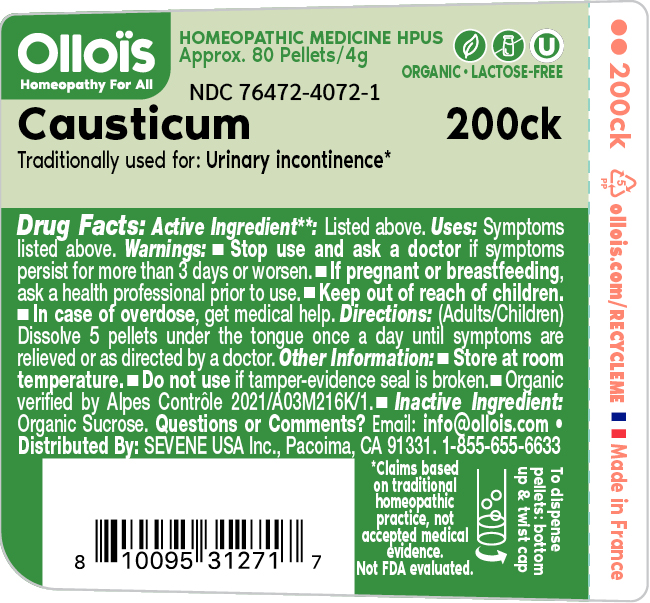 DRUG LABEL: CAUSTICUM

NDC: 76472-4072 | Form: PELLET
Manufacturer: SEVENE USA
Category: homeopathic | Type: HUMAN OTC DRUG LABEL
Date: 20250210

ACTIVE INGREDIENTS: CAUSTICUM 200 [hp_C]/1 1
INACTIVE INGREDIENTS: SUCROSE

Sevene USA (as PLD) - CAUSTICUM 200CK (76472-4072)

ACTIVE INGREDIENT

CAUSTICUM 200ck

TRADITIONALLY USED FOR:

URINARY INCONTINENCE

DIRECTIONS:

(adults/children) Dissolve 5 pellets under the tongue 3 times a day until symptoms are relieved or as directed by a doctor.

USE

TRADITIONALLY USED FOR: URINARY INCONTINENCE*

*CLAIMS BASED ON TRADITIONAL HOMEOPATHIC PRACTICE, NOT ACCEPTED MEDICAL EVIDENCE. NOT FDA EVALUATED.

WARNINGS

Stop use and ask a physician if symptoms persist for more than 3 days or worsen.

PREGNANCY OR BREAST FEEDING

If pregnant or breast-feeding, ask a health professional before use.

Keep out of reach of children.

In case of overdoes, get medical help.

OTHER INFORMATION

Store at room temperature.

Do not use if tamper-evidence seal is broken.

INACTIVE INGREDIENT

ORGANIC SUCROSE

ORGANIC VERIFIED BY ALPES CONTROLE 2021/A03M216K/1.

QUESTIONS OR COMMENTS?

EMAIL: INFO@OLLOIS.COM